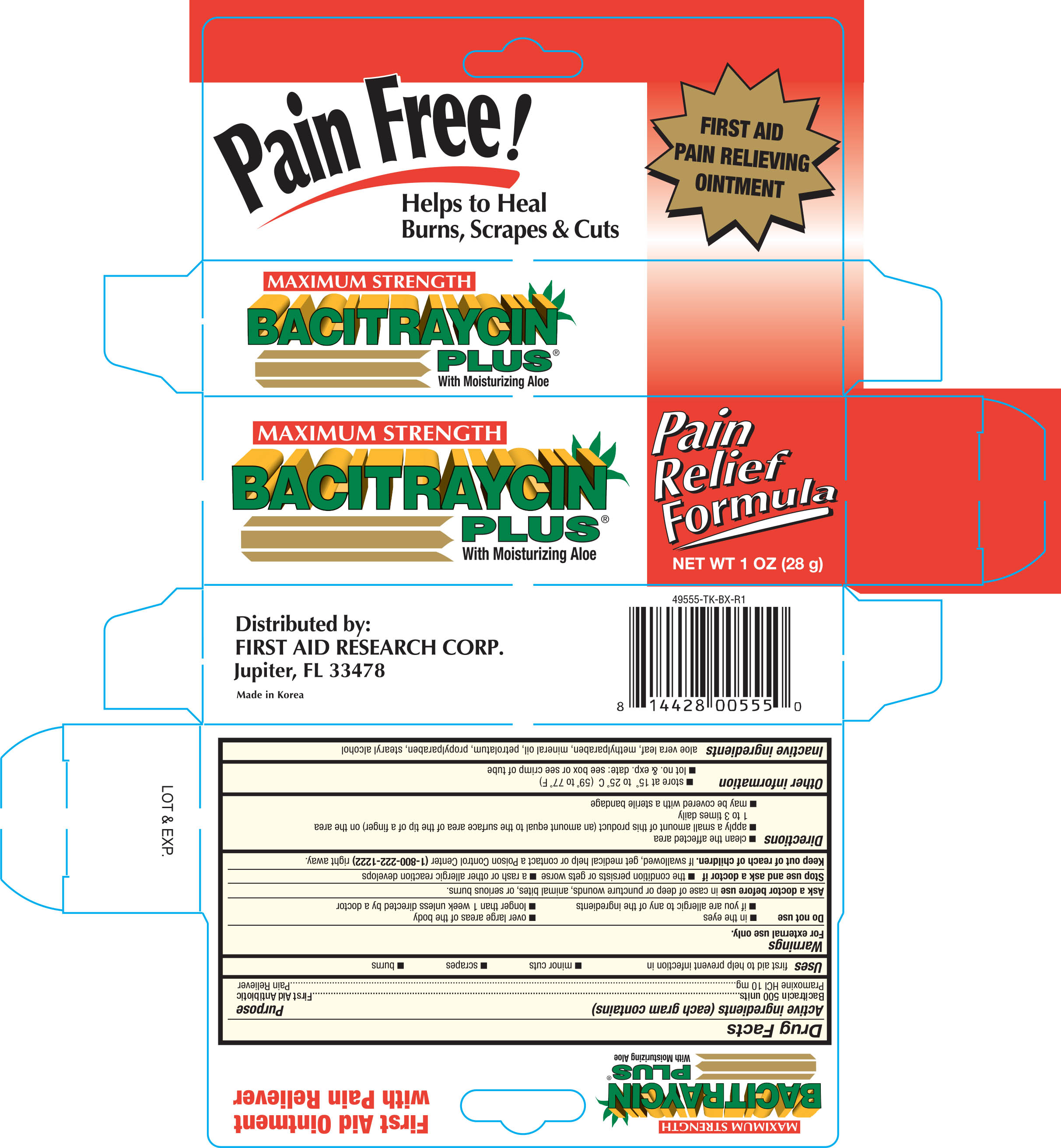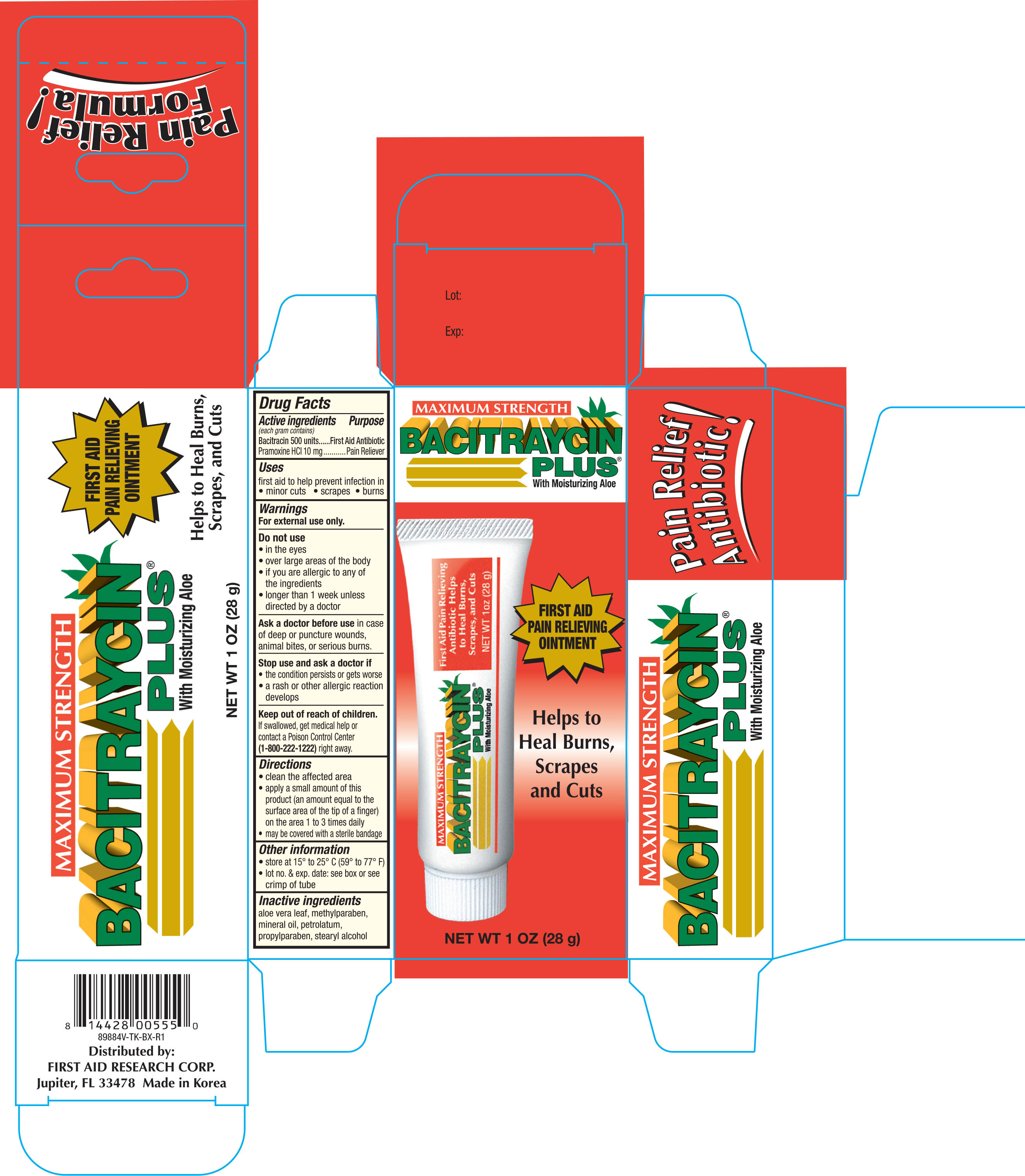 DRUG LABEL: First Aid Maximum Strength Bacitraycin Plus
NDC: 75983-055 | Form: OINTMENT
Manufacturer: First Aid Research Corp
Category: otc | Type: HUMAN OTC DRUG LABEL
Date: 20180301

ACTIVE INGREDIENTS: BACITRACIN 500 [USP'U]/1 g; PRAMOXINE HYDROCHLORIDE 10 mg/1 g
INACTIVE INGREDIENTS: METHYLPARABEN; ALOE VERA LEAF; MINERAL OIL; PETROLATUM; PROPYLPARABEN; STEARYL ALCOHOL

First Aid Maximum Strength Bacitraycin Plus Ointment 1oz 49555 (2018)

Active ingredients (each gram contains) Purpose

Bacitracin 500 units.......................................................................................................First Aid Antibiotic

Pramoxine HCI 10 mg..................................................................................................Pain Reliever

Uses

first aid to help prevent infection in

- minor cuts
- scrapes
- burns

Warnings

For external use only.

Do not use

- in the eyes
- if you are allergic to any of the ingredients
- over large areas of the body
- longer than 1 week unless directed by a doctor

Ask a doctor before use in case of deep or puncture wounds, animal bites, or serious burns

Keep out of reach of children. If swallowed, get medical help or contact a Poison Control Center (1-800-222-1222) right away

Directions

- clean the affected area
- apply a small amount of this product (an amount equal to the surface area of the tip of a finger) on the area 1 to 3 times daily
- may be covered with a sterile bandage

Other information

- store at 15° to 25°C (59° to 77°F)
- lot no. & exp. date: see box or see crimp of tube

Inactive ingredients

aloe vera leaf, methylparaben, mineral oil, petrolatum, propylparaben, stearyl alcohol

DOSAGE AND ADMINISTRATION

Distributed by:

First Aid Research Corp.

Jupiter, FL 33478

Made in Korea